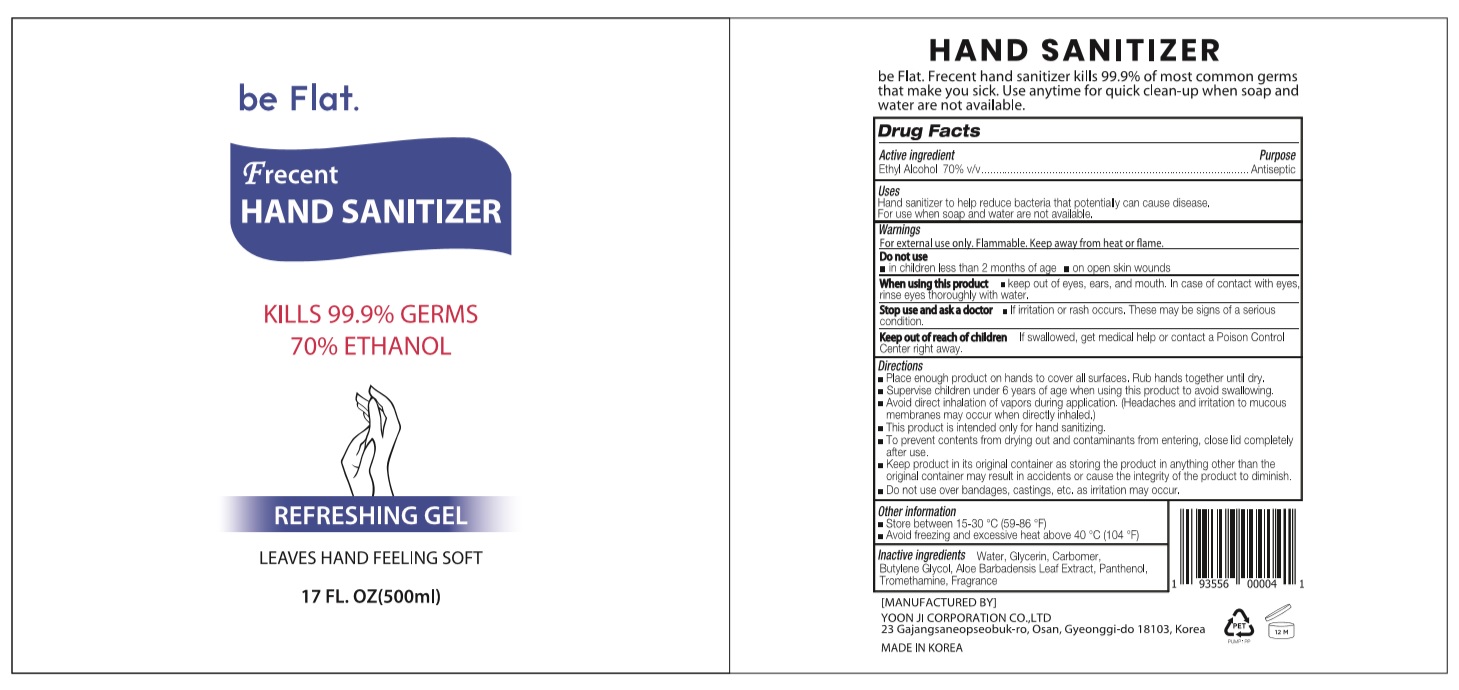 DRUG LABEL: be Flat. Frecent HAND SANITIZER
NDC: 75024-570 | Form: GEL
Manufacturer: YOON JI CORPORATION CO.,LTD
Category: otc | Type: HUMAN OTC DRUG LABEL
Date: 20200518

ACTIVE INGREDIENTS: ALCOHOL 350 mL/500 mL
INACTIVE INGREDIENTS: ALOE VERA LEAF; GLYCERIN; BUTYLENE GLYCOL; CARBOMER HOMOPOLYMER, UNSPECIFIED TYPE; WATER; PANTHENOL; TROMETHAMINE

be Flat. Frecent HAND SANITIZER : 75024-570-01